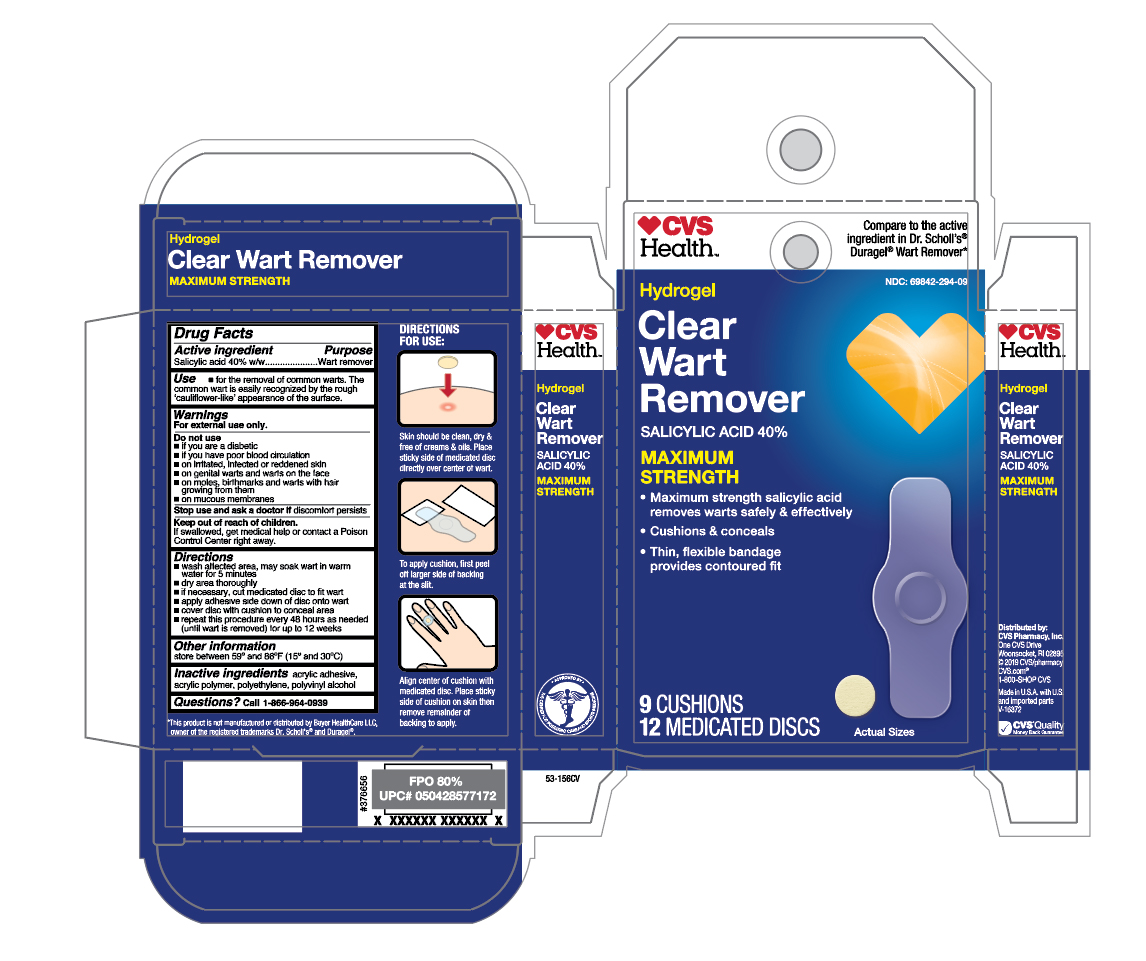 DRUG LABEL: Salicylic Acid
NDC: 69842-294 | Form: PATCH
Manufacturer: CVS Pharmacy
Category: otc | Type: HUMAN OTC DRUG LABEL
Date: 20241112

ACTIVE INGREDIENTS: SALICYLIC ACID 40 mg/12 1
INACTIVE INGREDIENTS: HIGH DENSITY POLYETHYLENE; VINYL ACETATE; POLYVINYL ALCOHOL, UNSPECIFIED

CVS Hydrogel Clear Wart Remover

Active ingredient

Salicylic acid 40% w/w

Purpose

Wart remover

Use

- for the removal of common warts. The common wart is easily recognized by the rough 'cauliflower-like' appearance of the surface.

Warnings

For external use only.

Do not use

- if you are a diabetic
- if you have poor blood circulation
- on irritated, infected or reddened skin
- on genital warts and warts on the face
- on moles, birthmarks and warts with hair growing from them
- on mucous membranes

Stop use and ask a doctor if

discomfort persists

Keep out of reach of children.

If swallowed, get medical help or contact a Poison Control Center right away.

Directions

- wash affected area, may soak wart in warm water for 5 minutes
- dry area thoroughly
- if necessary, cut medicated disc to fit wart
- apply adhesive side down of disc onto wart
- cover disc with cushions to conceal area
- repeat this procedure every 48 hours as needed (until wart is removed) for up to 12 weeks

Other information

store between 59° and 86°F (15° and 30°C)

Inactive ingredients

acrylic adhesive, acrylic polymer, polyethylene, polyvinyl alcohol

Questions?

Call 1-866-964-0939

Principal Display Panel

CVS Health

Hydrogel

Clear

Wart

Remover

SALICYLIC ACID 40%

MAXIMUM

STRENGTH

- Maximum strength salicylic acid

removes warts safely & effectively

- Cushions & conceals
- Thin, flexible bandage

provides contoured fit

9 CUSHIONS

12 MEDICATED DISCS